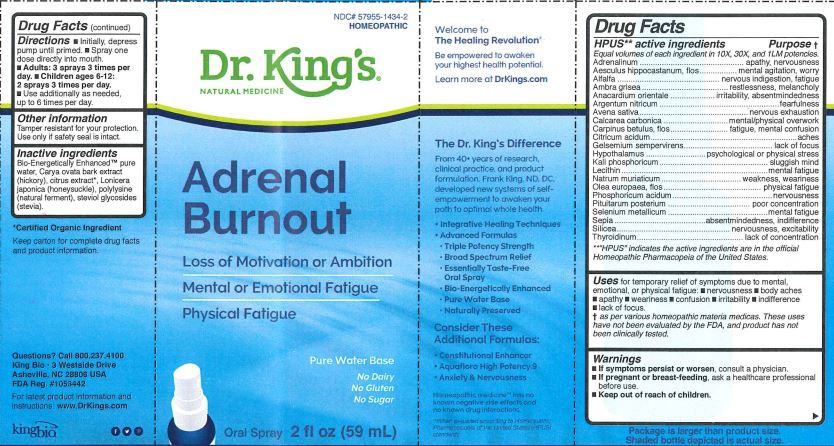 DRUG LABEL: Dr. Kings Natural Medicine
NDC: 57955-1434 | Form: LIQUID
Manufacturer: King Bio Inc.
Category: homeopathic | Type: HUMAN OTC DRUG LABEL
Date: 20190918

ACTIVE INGREDIENTS: EPINEPHRINE 10 [hp_X]/59 mL; AESCULUS HIPPOCASTANUM FLOWER 10 [hp_X]/59 mL; ALFALFA 10 [hp_X]/59 mL; AMBERGRIS 10 [hp_X]/59 mL; SEMECARPUS ANACARDIUM JUICE 10 [hp_X]/59 mL; SILVER NITRATE 10 [hp_X]/59 mL; AVENA SATIVA FLOWERING TOP 10 [hp_X]/59 mL; OYSTER SHELL CALCIUM CARBONATE, CRUDE 10 [hp_X]/59 mL; CARPINUS BETULUS FLOWERING TOP 10 [hp_X]/59 mL; ANHYDROUS CITRIC ACID 10 [hp_X]/59 mL; GELSEMIUM SEMPERVIRENS ROOT 10 [hp_X]/59 mL; BOS TAURUS HYPOTHALAMUS 10 [hp_X]/59 mL; POTASSIUM PHOSPHATE, DIBASIC 10 [hp_X]/59 mL; EGG PHOSPHOLIPIDS 10 [hp_X]/59 mL; SODIUM CHLORIDE 10 [hp_X]/59 mL; OLEA EUROPAEA FLOWER 10 [hp_X]/59 mL; PHOSPHORIC ACID 10 [hp_X]/59 mL; SUS SCROFA PITUITARY GLAND, POSTERIOR 10 [hp_X]/59 mL; SELENIUM 10 [hp_X]/59 mL; SEPIA OFFICINALIS JUICE 10 [hp_X]/59 mL; SILICON DIOXIDE 10 [hp_X]/59 mL; THYROID, UNSPECIFIED 10 [hp_X]/59 mL
INACTIVE INGREDIENTS: WATER; CARYA OVATA BARK; CITRUS BIOFLAVONOIDS; LONICERA JAPONICA FLOWER; POLYEPSILON-LYSINE (4000 MW); REBAUDIOSIDE A

Adrenal Burnout

Warnings

- If sypmtoms persist or worsen, consult a physician.
- If pregnant or breast-feeding, take only on advice of a healthcare professional before use.

Keep out of reach of children.

Directions

- Initially, depress pump until primed.
- Spray one dose directly into mouth.
- Adults: 3 sprays 3 times per day.
- Children ages 6-12 years: 2 sprays 3 times per day.
- Use additionally as needed, up to 6 times per day.

Other Information

Tamper resistant for your protection. Use only if safety seal is intact.

HPUS** active ingredients

Adrenalinum, Aesculus hippocastanum, flos, Alfalfa, Ambra grisea, Anacardium orientale, Argentum nitricum, Avena sativa, Calcarea carbonica, Carpinus betulus, flos, Citricum acidum, Gelsemium sempervirens, Hypothalamus, Kali phosphoricum, Lecithin, Natrum muriaticum, Olea europaea, flos, Phosphoricum acidum, Pituitarum posterium, Selenium metallicum, Sepia, Silicea, Thyroidinum.

volumes of each ingredient in 10X, 30X, 100X, 1LM potencies.

**HPUS indicates the active ingredints are in the official Homeopathic Pharmacopeia of the United States.

Purpose

Adrenalinum...Apathy,nervousness

Aesculus hippocastanum, flos...mental agitation, worry

Alfalfa...nervous indigestion, fatigue

Ambra grisea...restlessness, melancholy

Anacardium orientale...irritability, absentmindedness

Argentum nitricum...fearfulness

Avena sativa...nervous exhausion

Calcarea carbonica...mental/physical overwork

Carpinus betulus, flos...fatigue, mental confusion

Citricum acidum...aches

Gelsemium sempervirens...lack of focus

Hypothalamus...psychological or physical stress

Kali phosphoricum...sluggish mind

Lecithin...mental fatigue

Natrum muriaticum...weakness,weariness

Olea europaea, flos...physical fatigue

Phosphoricum acidum...nervousness

Pituitarum posterium...poor concentration

Selenium metallicum...mental fatigue

Sepia...absentmindedness, indifference

Silicea...nervousness, excitability

Thyroidinum...lack of concentration

Inactive Ingredients

Bio-Energetically Enhanced™ pure water, Carya ovata bark extract (hickory), citrus extract, Lonicera japonica (honeysuckle), polylysine (natural ferment), steviol glycosides(stevia).

Uses

Uses for temporary relief of symptoms due to mental, emotional, or physical fatigue:

- nervousness
- body aches
- apathy
- weariness
- confusion
- irritability
- indifference
- lack of focus